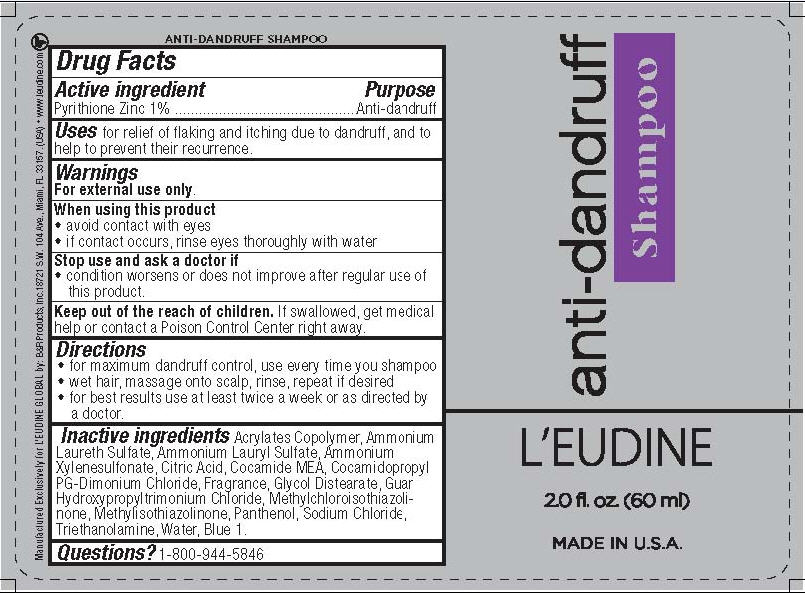 DRUG LABEL: LEudine Anti-dandruff
NDC: 76482-013 | Form: SHAMPOO
Manufacturer: B&R Products Inc
Category: otc | Type: HUMAN OTC DRUG LABEL
Date: 20130213

ACTIVE INGREDIENTS: PYRITHIONE ZINC 1 g/100 mL
INACTIVE INGREDIENTS: ETHYL ACRYLATE AND METHYL METHACRYLATE COPOLYMER (2:1; 600000 MW); AMMONIUM LAURETH-2 SULFATE; AMMONIUM LAURYL SULFATE; AMMONIUM XYLENESULFONATE; CITRIC ACID MONOHYDRATE; COCO MONOETHANOLAMIDE; COCAMIDOPROPYL PG-DIMONIUM CHLORIDE; GLYCOL DISTEARATE; GUAR HYDROXYPROPYLTRIMONIUM CHLORIDE (1.7 SUBSTITUENTS PER SACCHARIDE); METHYLCHLOROISOTHIAZOLINONE; METHYLISOTHIAZOLINONE; PANTHENOL; SODIUM CHLORIDE; TROLAMINE; WATER; FD&C BLUE NO. 1

L'Eudine Anti-dandruff Shampoo

Active ingredient

Pyrithione Zinc 1%

Purpose

Anti-dandruff

Keep Out of Reach of Children

If swallowed, get medical help or contact a Poison Control Center right away.

Uses

for relief of flaking and itching due to dandruff, and to help prevent their recurrence.

Warnings

For external use only.

When using this product

- avoid contact with eyes
- if contact occurs, rinse eyes thoroughly with water

Stop use and ask a doctor if

- condition worsens or does not improve after regular use of this product.

Directions

- for maximum dandruff control, use every time you shampoo
- wet hair, massage onto scalp, rinse, repeat if desired
- for best results use at least twice a week or as directed by a doctor.

Inactive ingredients

Acrylates Copolymer, Ammonium Laureth Sulfate, Ammonium Lauryl Sulfate, Ammonium Xylenesulfonate, Citric Acid, Cocamide MEA, Cocamidopropyl PG-Dimonium Chloride, Fragrance, Glycol Distearate, Guar Hydroxypropyltrimonium Chloride, Methylchloroisothiazolinone, Methylisothiazolinone, Panthenol, Sodium Chloride, Triethanolamine, Water, Blue 1.

Questions?

1-800-944-5846

Package/Label Principal Display Panel

L'EUDINE

anti-dandruff Shampoo

2.0 fl. oz. (60 mL)

MADE IN USA

Bottle Label